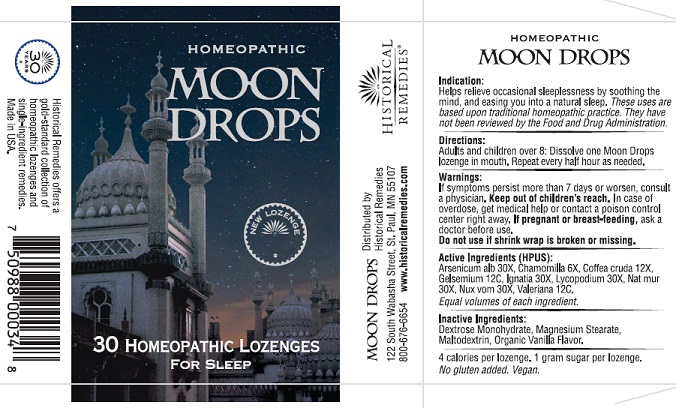 DRUG LABEL: Homeopathic Moon drops
NDC: 57556-008 | Form: LOZENGE
Manufacturer: Historical Remedies LLP
Category: otc | Type: HUMAN OTC DRUG LABEL
Date: 20251007

ACTIVE INGREDIENTS: ARSENIC TRIOXIDE 30 [hp_X]/1 1; MATRICARIA CHAMOMILLA WHOLE 6 [hp_X]/1 1; ARABICA COFFEE BEAN 12 [hp_X]/1 1; GELSEMIUM SEMPERVIRENS ROOT 12 [hp_C]/1 1; STRYCHNOS IGNATII SEED 30 [hp_X]/1 1; LYCOPODIUM CLAVATUM SPORE 30 [hp_X]/1 1; SODIUM CHLORIDE 30 [hp_X]/1 1; STRYCHNOS NUX-VOMICA SEED 30 [hp_X]/1 1; VALERIAN 12 [hp_C]/1 1
INACTIVE INGREDIENTS: DEXTROSE MONOHYDRATE; MAGNESIUM STEARATE; MALTODEXTRIN; ACHLYS TRIPHYLLA WHOLE

Indication

Helps relieve occasional sleeplessness by soothing the mind, and easing you into a natural sleep. These uses are based upon traditional homeopathic practice. They have not been reviewed by the Food and Drug Administration.

Directions

Adults and children over 8: Dissolve one Moon Drops lozenge in mouth. Repeat every half hour as needed.

Warnings

If symptoms persist more than 7 days or worsen, consult a physician. Keep out of children’s reach.In case of overdose, get medical help or contact a poison control center right away. I f pregnant or breast-feeding, ask a doctor before use.
Do not use if shrink wrap is broken or missing.

Active Ingredients (HPUS)

Arsenicum alb 30X, Chamomilla 6X, Coffea cruda 12X, Gelsemium 12C, Ignatia 30X, Lycopodium 30X, Nat mur 30X, Nux vom 30X, Valeriana 12C.

Inctive Ingredients

Dextrose Monohydrate, Magnesium Stearate, Maltodextrin, Organic Vanilla Flavor.